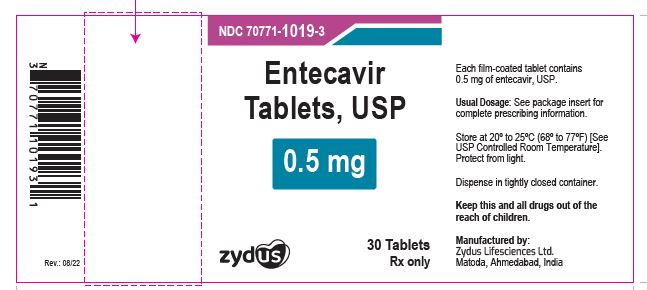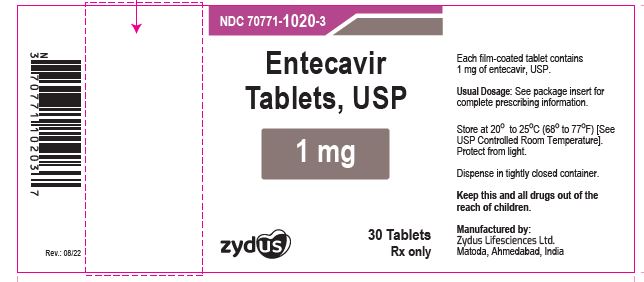 DRUG LABEL: Entecavir
NDC: 70771-1019 | Form: TABLET, FILM COATED
Manufacturer: Zydus Lifesciences Limited
Category: prescription | Type: HUMAN PRESCRIPTION DRUG LABEL
Date: 20241128

ACTIVE INGREDIENTS: ENTECAVIR 0.5 mg/1 1
INACTIVE INGREDIENTS: CELLULOSE, MICROCRYSTALLINE; CROSPOVIDONE; HYPROMELLOSES; LACTOSE MONOHYDRATE; MAGNESIUM STEARATE; POLYETHYLENE GLYCOL, UNSPECIFIED; TALC; TITANIUM DIOXIDE

ENTECAVIR TABLETS

PACKAGE LABEL.PRINCIPAL DISPLAY PANEL

NDC 70771-1019-3

Entecavir Tablets USP, 0.5 mg

Rx Only

30 tablets

NDC 70771-1020-3

Entecavir Tablets USP, 1 mg

Rx Only

30 tablets